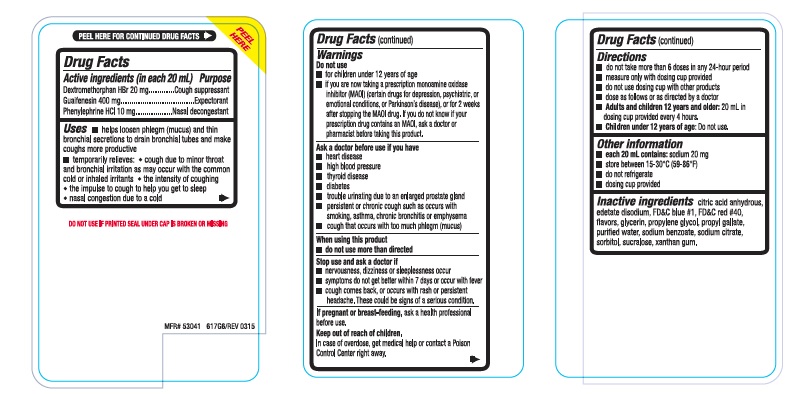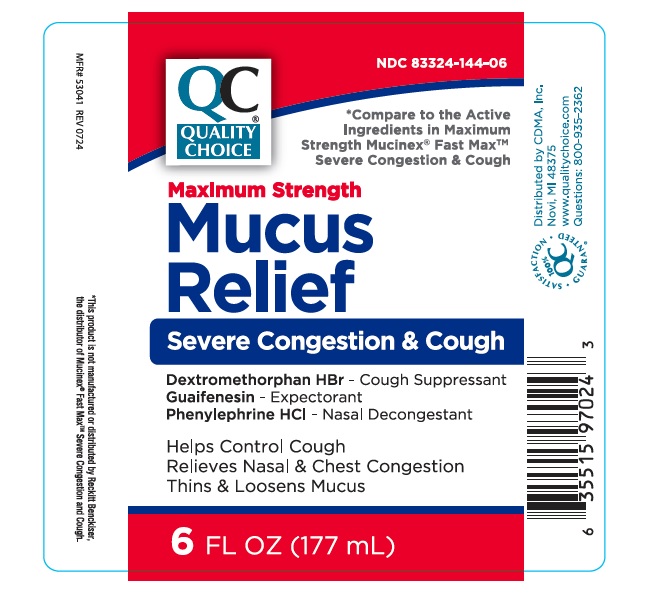 DRUG LABEL: QCH Maximum Strength Mucus Relief 617
NDC: 83324-144 | Form: LIQUID
Manufacturer: Chain Drug Marketing Association Inc.
Category: otc | Type: Human OTC Drug Label
Date: 20240906

ACTIVE INGREDIENTS: DEXTROMETHORPHAN HYDROBROMIDE 20 mg/20 mL; GUAIFENESIN 400 mg/20 mL; PHENYLEPHRINE HYDROCHLORIDE 10 mg/20 mL
INACTIVE INGREDIENTS: ANHYDROUS CITRIC ACID; EDETATE DISODIUM; FD&C BLUE NO. 1; FD&C RED NO. 40; GLYCERIN; PROPYLENE GLYCOL; PROPYL GALLATE; WATER; SODIUM BENZOATE; SODIUM CITRATE, UNSPECIFIED FORM; SORBITOL; SUCRALOSE; XANTHAN GUM

QCH Maximum Strength Mucus Relief 617

ACTIVE INGREDIENTS (in each 20 mL)

Dextromethorphan HBr 20 mg
Guaifenesin 400 mg
Phenylephrine HCI 10 mg

PURPOSE

Cough suppressant

Expectorant

Nasal decongestant

USE(S)

• helps loosen phlegm (mucus) and thin bronchial secretions to drain bronchial tubes and make coughs more productive
• temporarily relieves:

• cough due to minor throat and bronchial irritation as may occur with the common cold or inhaled irritants

• the intensity of coughing
• the impulse to cough to help you get to sleep
• nasal congestion due to a cold

WARNINGS

.

DO NOT USE

• for children under 12 years of age
• if you are now taking a prescription monoamine oxidase inhibitor (MAOI) (certain drugs for depression, psychiatric, or emotional conditions, or Parkinson's disease), or for 2 weeks after stopping the MAOI drug. If you do not know if your prescription drug contains an MAOI, ask a doctor or
pharmacist before taking this product.

ASK A DOCTOR BEFORE USE IF YOU HAVE

• heart disease
• high blood pressure
• thyroid disease
• diabetes
• trouble urinating due to an enlarged prostate gland
• persistent or chronic cough such as occurs with smoking, asthma, chronic bronchitis or emphysema
• cough that occurs with too much phlegm (mucus)

WHEN USING THIS PRODUCT

• do not use more than directed

STOP USE AND ASK DOCTOR IF

- nervousness, dizziness or sleeplessness occur
- symptoms do not get better within 7 days or occur with fever
- cough comes back, or occurs with rash or persistent headache. These could be signs of a serious condition.

PREGNANCY/BREASTFEEDING

ask a health professional before use.

KEEP OUT OF REACH OF CHILDREN

In case of overdose, get medical help or contact a Poison Control Center right away.

DIRECTIONS

• do not take more than 6 doses in any 24-hour period
• measure only with dosing cup provided
• do not use dosing cup with other products
• dose as follows or as directed by a doctor
• Adults and children 12 years and older: 20 ml in dosing cup provided every 4 hours .
• Children under 12 years of age: Do not use

OTHER INFORMATION

• each 20 ml contains: sodium 20 mg
• store between 15-30ºC (59-86ºF)
• do not refrigerate
• dosing cup provided

INACTIVE INGREDIENTS

citric acid anhydrous, edetate disodium, FD&C blue #1, FD&C red #40, flavors, glycerin, propylene glycol, propyl gallate, purified water, sodium benzoate, sodium citrate, sorbitol, sucralose, xanthan gum.

PRINCIPAL DISPLAY PANEL

NDC 83324-144-06

QC® QUALITY CHOICE

*Compare to the Active Ingredients in Maximum Strength Mucinex® Fax MaxTM Severe Congestion & Cough

Maximum Strength Mucus Relief Sever Congestion & Cough

Dextromethorphan HBr 20 mg - Cough suppressant
Guaifenesin 400 mg - Expectorant
Phenylephrine HCI 10 mg - Nasal decongestant

Helps Control Cough
Relieves Nasal & Chest Congestion
Thins & Loosens Mucus

6 FL OZ (177 mL)